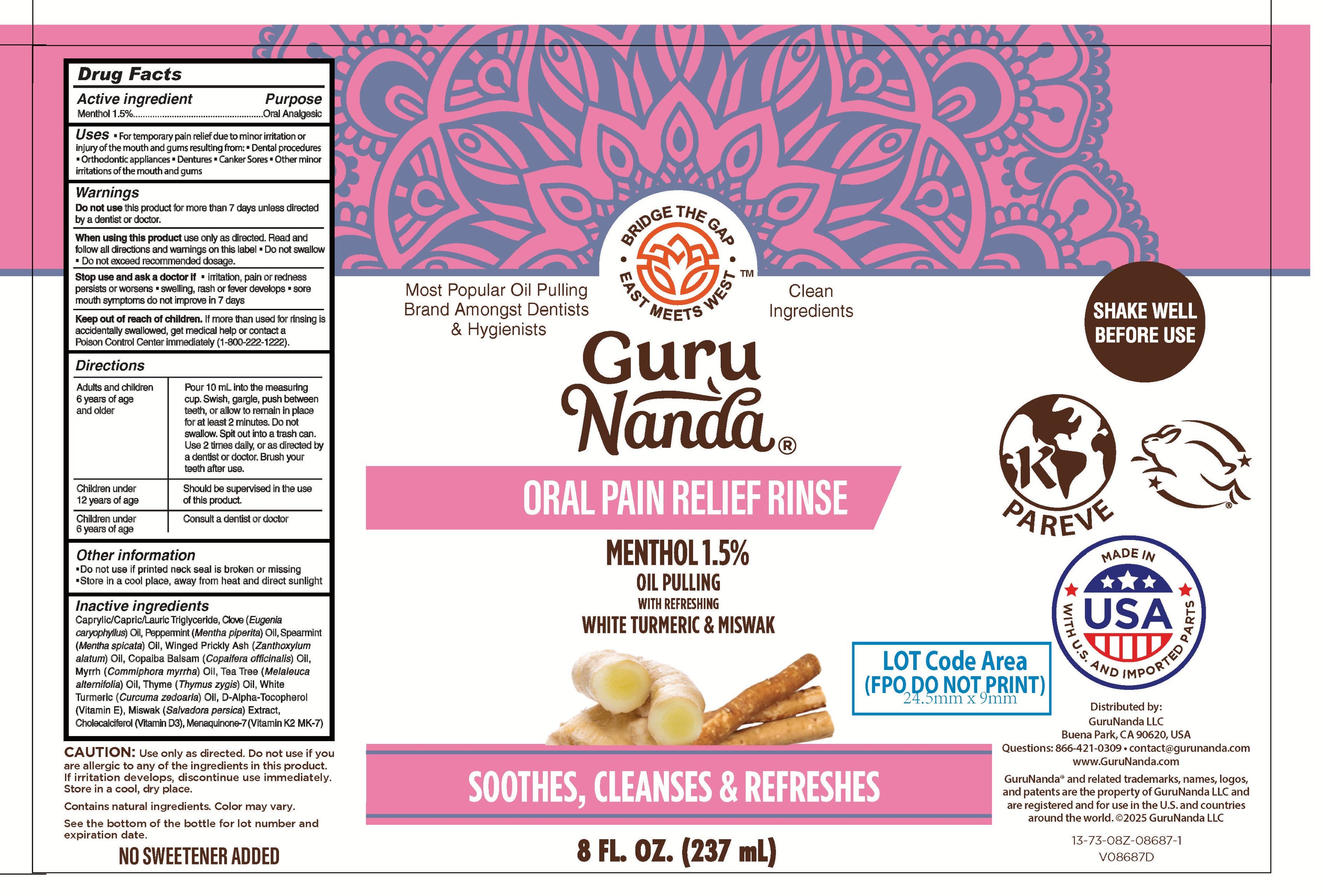 DRUG LABEL: GuruNanda Oral Pain Relief
NDC: 70708-011 | Form: RINSE
Manufacturer: GURUNANDA, LLC
Category: otc | Type: HUMAN OTC DRUG LABEL
Date: 20251111

ACTIVE INGREDIENTS: LEVOMENTHOL 15 mg/1 mL
INACTIVE INGREDIENTS: ZANTHOXYLUM ARMATUM FRUIT; THYME OIL; .ALPHA.-TOCOPHEROL, D-; CHOLECALCIFEROL; MENTHA PIPERITA (PEPPERMINT) OIL; TEA TREE OIL; MYRRH OIL; CAPRYLIC/CAPRIC/LAURIC TRIGLYCERIDE; CLOVE OIL; SPEARMINT OIL; MENAQUINONE-7; SALVADORA PERSICA WHOLE; COPAIFERA OFFICINALIS (BALSAM COPAIBA) RESIN; CURCUMA ZEDOARIA OIL

GuruNanda Oral Pain Relief Rinse Sensitive

ACTIVE INGREDIENT

Menthol 1.5%

PURPOSE

Oral Analgesic

Uses

- For temporary pain relief due to minor irritation or injury of the mouth and gums resulting from:
- Dental procedures
- Orthodontic appliances
- Dentures
- Canker Sores
- Other minor irritations of the mouth and gums

Warnings

Do not use

this product for more than 7 days unless directed by a dentist or doctor.

When using this product

use only as directed. Read and follow all directions and warnings on this label.

- Do not swallow
- Do not exceed recommended dosage.

Stop use and ask doctor if

- irritation, pain or redness persists or worsens
- swelling, rash or fever devleops
- sore mouth symptoms do not improve in 7 days

Keep out of reach of children.

If more than used for rinsing is accidentally swallowed, get medical help or contact a Poison Control Center immediately (1-800-222-1222).

Directions

Adults and children 6 years of age and older: Pour 10 mL into the measuring cup. Swish, gargle, push between teeth, or allow to remain in place for at least 2 minutes. Do not swallow. Spit out into a trash can. Use up to twice daily, or as directed by a dentist or doctor. Brush your teeth after use.

Children under 12 years of age: Should be supervised in the use of this product.
Children under 6 years of age: Consult a dentist or doctor

Other information

- Do not use if pritned neck seal is broken or missing
- Store in a cool place, away from heat and direct sunlight

Inactive ingredients

Caprylic/Capric/Lauric Triglyceride, Clove (Eugenia caryophyllus) Oil, Peppermint (Mentha piperita) Oil, Spearmint (Mentha spicata) Oil, Winged Prickly Ash (Zanthoxylum alatum) Oil, Copaiba Balsam (Copaifera officinalis) Oil, Myrrh (Commiphora myrrha) Oil, Tea Tree (Melaleuca alternifolia) Oil, Thyme (Thymus zygis) Oil, White Tumeric (Curcuma zedoaria) Oil, D-Alpha-Tocopherol (Vitamin E), Miswak (Salvadora persica) Extract, Cholecalciferol (Vitamin D3), Menaquinone-7 (Vitamin K2 MK-7)